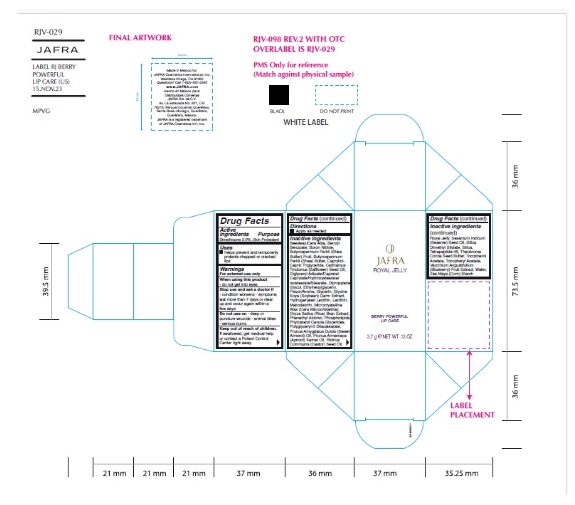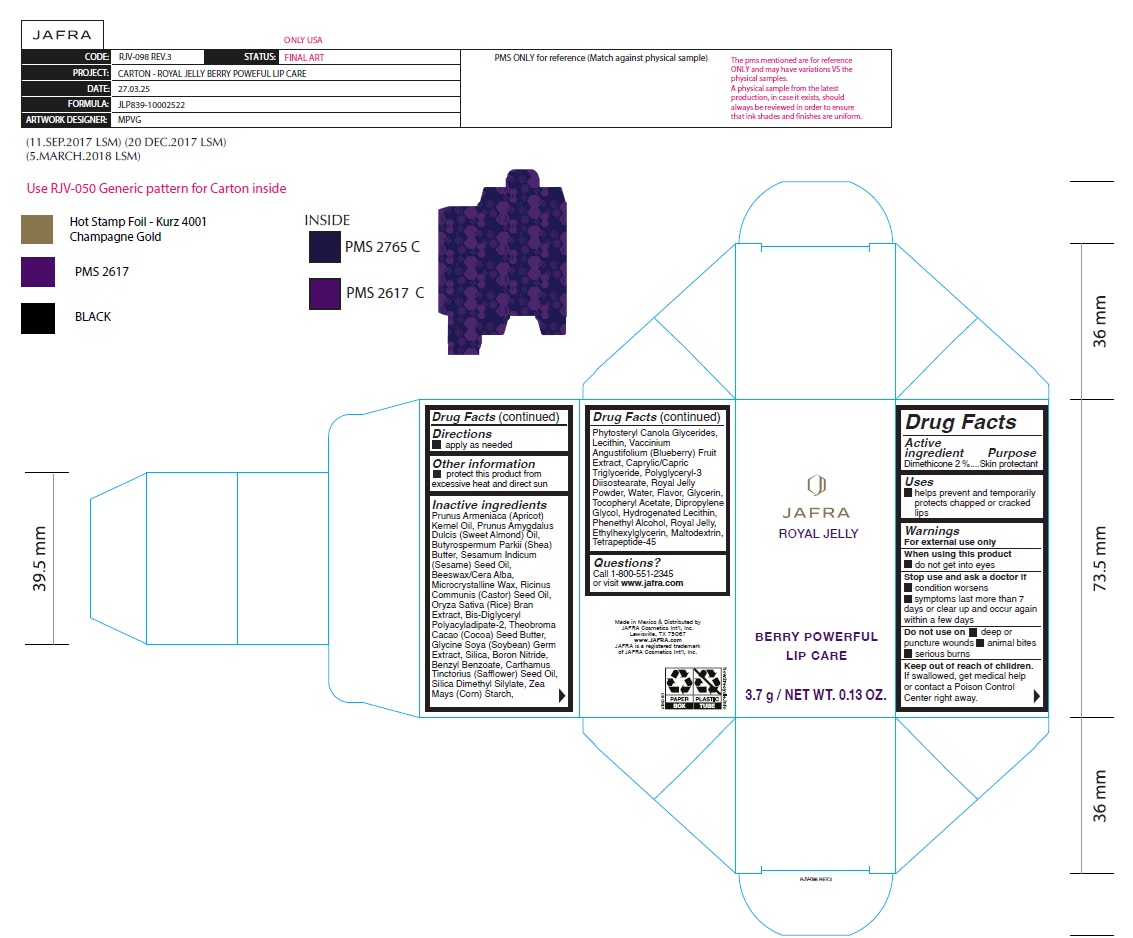 DRUG LABEL: Royal Jelly Berry Powerful Lip Care
NDC: 68828-704 | Form: STICK
Manufacturer: Distribuidora Comercial Jafra, S.A. de C.V.
Category: otc | Type: HUMAN OTC DRUG LABEL
Date: 20251105

ACTIVE INGREDIENTS: DIMETHICONE 2 g/100 g
INACTIVE INGREDIENTS: BORON NITRIDE; SHEA BUTTER; MEDIUM-CHAIN TRIGLYCERIDES; SAFFLOWER OIL; DIPROPYLENE GLYCOL; ETHYLHEXYLGLYCERIN; GLYCERIN; SOYBEAN GERM; HYDROGENATED SOYBEAN LECITHIN; LECITHIN, SOYBEAN; MALTODEXTRIN; MICROCRYSTALLINE WAX; RICE BRAN; PHENYLETHYL ALCOHOL; POLYGLYCERYL-3 DIISOSTEARATE; ALMOND OIL; APRICOT KERNEL OIL; CASTOR OIL; SILICA DIMETHYL SILYLATE; SILICON DIOXIDE; COCOA BUTTER; .ALPHA.-TOCOPHEROL ACETATE; LOWBUSH BLUEBERRY; WATER; STARCH, CORN; WHITE WAX; ROYAL JELLY; SESAME OIL; BENZYL BENZOATE; BIS-DIGLYCERYL POLYACYLADIPATE-2

Royal Jelly Berry Powerful Lip Care

Active ingredient

Dimethicone 2.0%

Purpose

Skin Protectant

Uses

• Helps prevent and temporarily protects chapped or cracked lips

Warnings

For external use only

When using this product do not get into eyes

Stop use and ask a doctor if
• condition worsens
• symptoms last more than 7 days or clear up and occur again within a few days
Do not use on
• deep or puncture wounds
• animal bites
• serious burns

Keep out of reach of children.If swallowed, get medical help or contact a Poison Control center right away.

Directions

- Apply as needed

Inactive ingredients

Prunus Armeniaca (Apricot) Kernel Oil, Prunus Amygdalus Dulcis (Sweet Almond) Oil, Butyrospermum Parkii (Shea) Butter, Sesamum Indicum (Sesame) Seed Oil, Beeswax/Cera Alba, Microcrystalline Wax, Ricinus Communis (Castor) Seed Oil, Oryza Sativa (Rice) Bran Extract, Bis-Diglyceryl Polyacyladipate-2, Theobroma Cacao (Cocoa) Seed Butter, Glycine Soya (Soybean) Germ Extract, Silica, Boron Nitride, Benzyl Benzoate, Carthamus Tinctorius (Safflower) Seed Oil, Silica Dimethyl Silylate, Zea Mays (Corn) Starch, Phytosteryl Canola Glycerides, Lecithin, Vaccinium Angustifolium (Blueberry) Fruit Extract, Caprylic/Capric Triglyceride, Polyglyceryl-3 Diisostearate, Royal Jelly Powder, Water, Flavor, Glycerin, Tocopheryl Acetate, Dipropylene Glycol, Hydrogenated Lecithin, Phenethyl Alcohol, Royal Jelly, Ethylhexylglycerin, Maltodextrin, Tetrapeptide-45